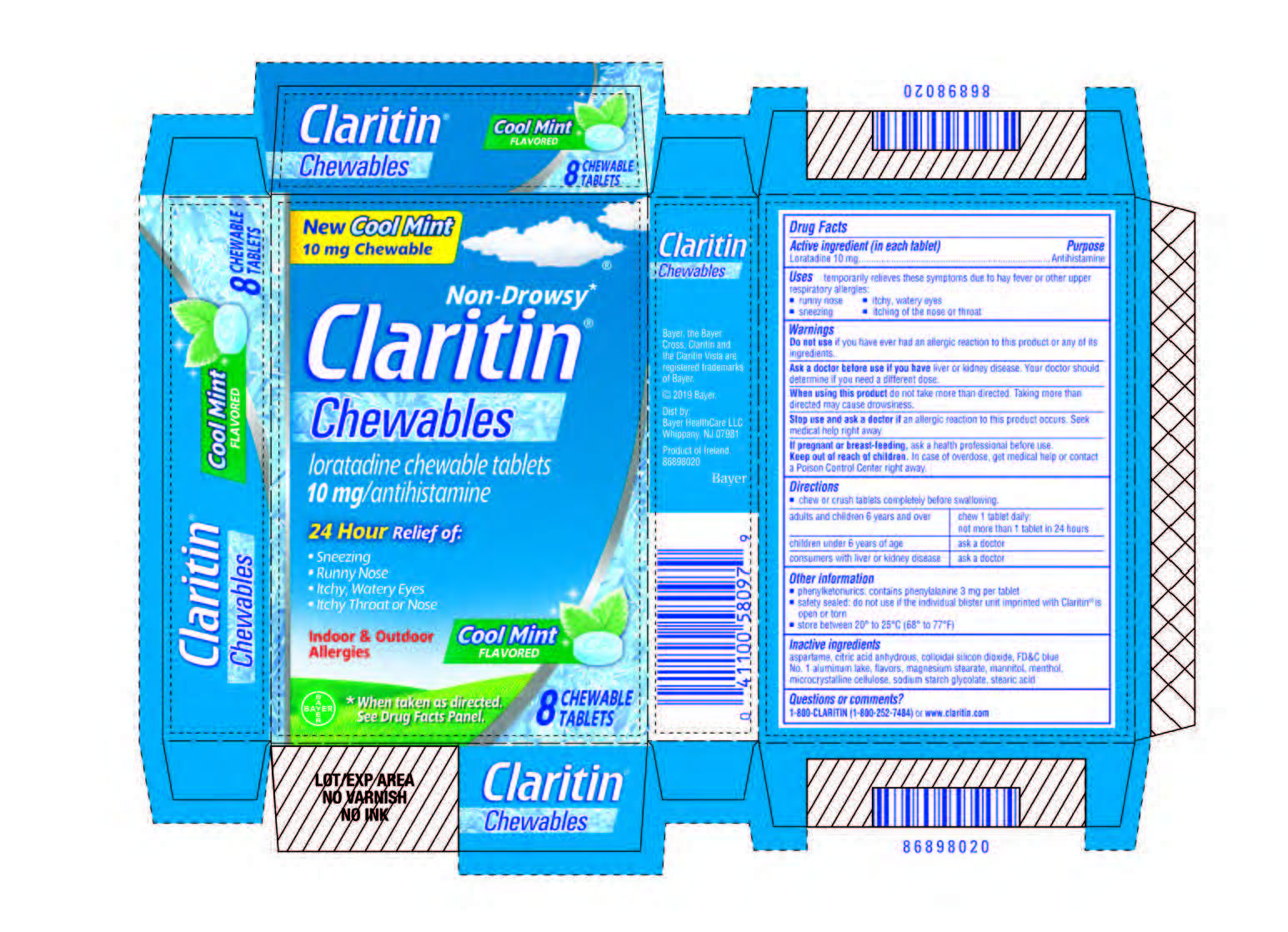 DRUG LABEL: Claritin Chewable
NDC: 11523-4364 | Form: TABLET, CHEWABLE
Manufacturer: Bayer HealthCare LLC.
Category: otc | Type: HUMAN OTC DRUG LABEL
Date: 20251205

ACTIVE INGREDIENTS: LORATADINE 10 mg/1 1
INACTIVE INGREDIENTS: SODIUM STARCH GLYCOLATE TYPE A CORN; STEARIC ACID; MAGNESIUM STEARATE; SILICON DIOXIDE; FD&C BLUE NO. 1--ALUMINUM LAKE; MENTHOL; ANHYDROUS CITRIC ACID; ASPARTAME; MANNITOL; MICROCRYSTALLINE CELLULOSE

Claritin 10mg Cool Mint Chewable (1613932)

Drug Facts

Active ingredient

Loratadine

Purpose

Antihistamine

Uses

Uses temporarily relieves these symptoms due to hay fever or other upper respiratory allergies:

• runny nose

• itchy, watery eyes

• sneezing

• itching of the nose or throat

Warnings

Do not use if you have ever had an allergic reaction to this product or any of its ingredients.

Ask a doctor before use if you have liver or kidney disease. Your doctor should determine if you need a different

dose.

When using this product do not take more than directed. Taking more than directed may cause drowsiness.

Stop use and ask a doctor if an allergic reaction to this product occurs. Seek medical help right away.

PREGNANCY OR BREAST FEEDING

If pregnant or breast-feeding, ask a health professional before use.

Keep out of reach of children. In case of overdose, get medical help or contact a Poison Control Center right away.

Directions

• chew or crush tablets completely before swallowing

adults and children 6 years and over | chew 1 tablet daily; not more than 1 tablet in 24 hours
children under 6 years of age | ask a doctor
consumers with liver or kidney disease | ask a doctor

Other information

• phenylketonurics: contains phenylalanine 3 mg per tablet

• safety sealed: do not use if the individual blister unit imprinted with Claritin® is open or torn

• store between 20° to 25°C (68° to 77°F)

Inactive ingredients

anhydrous citric acid;aspartame;fd&c blue no. 1--aluminum lake;magnesium

stearate;mannitol;menthol;microcrystalline cellulose;silicon dioxide;sodium starch glycolate type a corn;stearic acid

Questions or comments

1-800-CLARITIN (1-800-252-7484) or www.claritin.com

Carton 8 count

New Cool Mint

10 mg Chewable

Non-Drowsy*

Claritin®

Chewables

loratadine chewable tablets

10 mg/antihistamine

24 Hour Relief of:

- Sneezing
- Runny Nose
- Itchy, Watery Eyes
- Itchy Throat or Nose

Indoor & Outdoor

Allergies

Cool Mint

Flavored

*When taken as directed.

See Drug Facts Panel.

8 Chewable Tablets